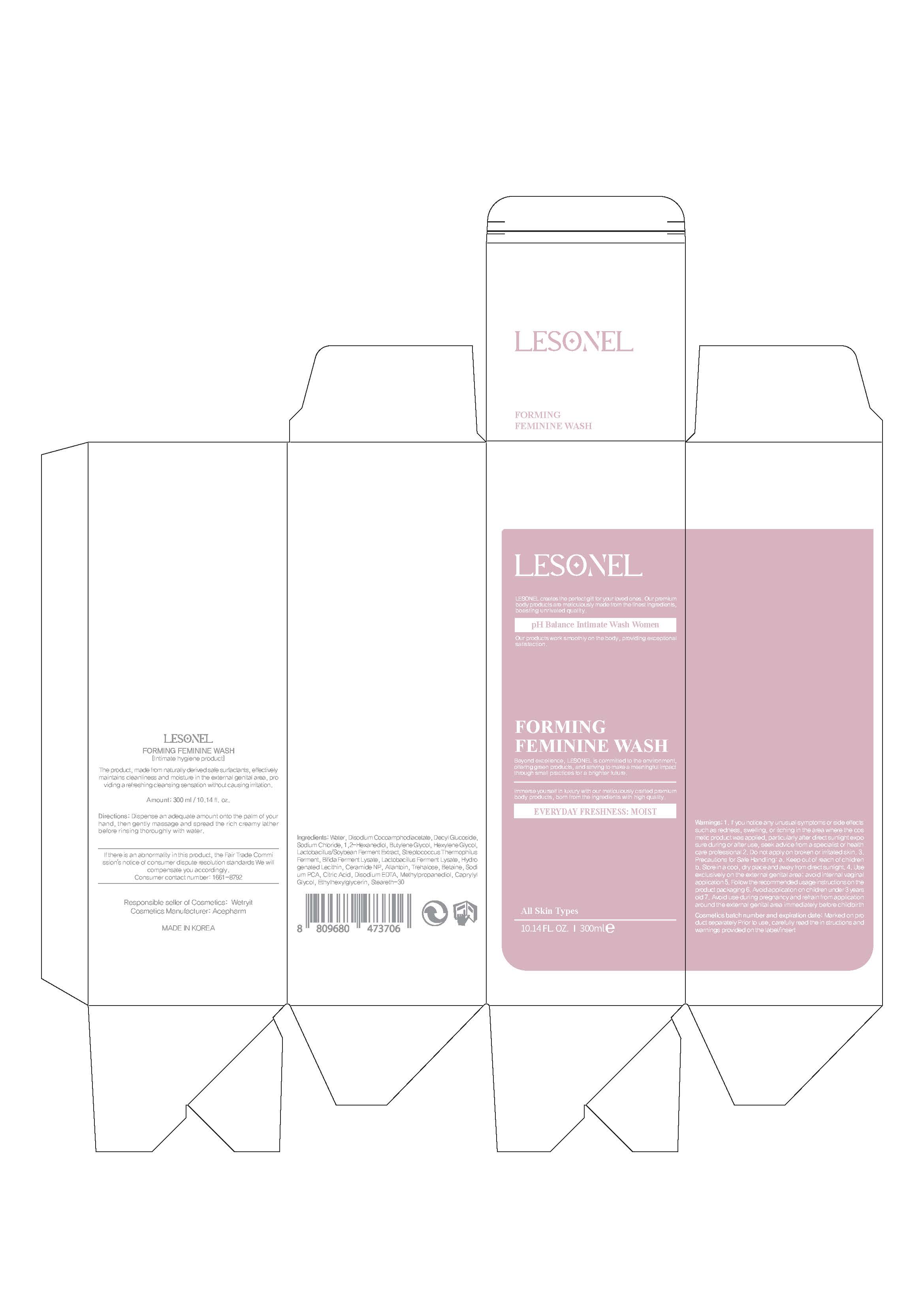 DRUG LABEL: LESONEL FORMING FEMININE WASH
NDC: 74196-0007 | Form: LIQUID
Manufacturer: ACE PHARMACEUTICAL CO LTD
Category: otc | Type: HUMAN OTC DRUG LABEL
Date: 20240117

ACTIVE INGREDIENTS: METHYLPROPANEDIOL 0.685 g/100 mL
INACTIVE INGREDIENTS: WATER; BUTYLENE GLYCOL

Drug Facts

ACTIVE INGREDIENT

METHYLPROPANEDIOL

INACTIVE INGREDIENT

Water
Disodium Cocoamphodiacetate
Decyl Glucoside
Sodium Chloride
1,2-Hexanediol
Butylene Glycol
Hexylene Glycol
Lactobacillus/Soybean Ferment Extract
Streptococcus Thermophilus Ferment
Bifida Ferment Lysate
Lactobacillus Ferment Lysate
Hydrogenated Lecithin
Ceramide NP
Allantoin
Trehalose
Betaine
Sodium PCA
Citric Acid
Disodium EDTA
Caprylyl Glycol
Ethylhexylglycerin
Steareth-30

PURPOSE

The product, made from naturally derivedsafesurfactants, effectively maintains cleanliness and moisturein the external genital area,

providingarefreshing cleansing sensation without causing irritation

KEEP OUT OF REACH OF THE CHILDREN

INDICATIONS AND USAGE

Dispense an adequate amount onto the palm of your hand, then gently massage and spread the rich creamy lather before rinsing thoroughly with water.

WARNINGS

1. If you notice any unusual symptoms or side effects such as redness, swelling, or itching in the area where the cos metic product was applied, particularly after direct sunlight expo sure during or after use, seek advice from a specialist or health care professional

2. Do not apply on broken or irritated skin.

3. Precautions for Safe Handling: a. Keep out of reach of children

DOSAGE AND ADMINISTRATION

for vaginal use only